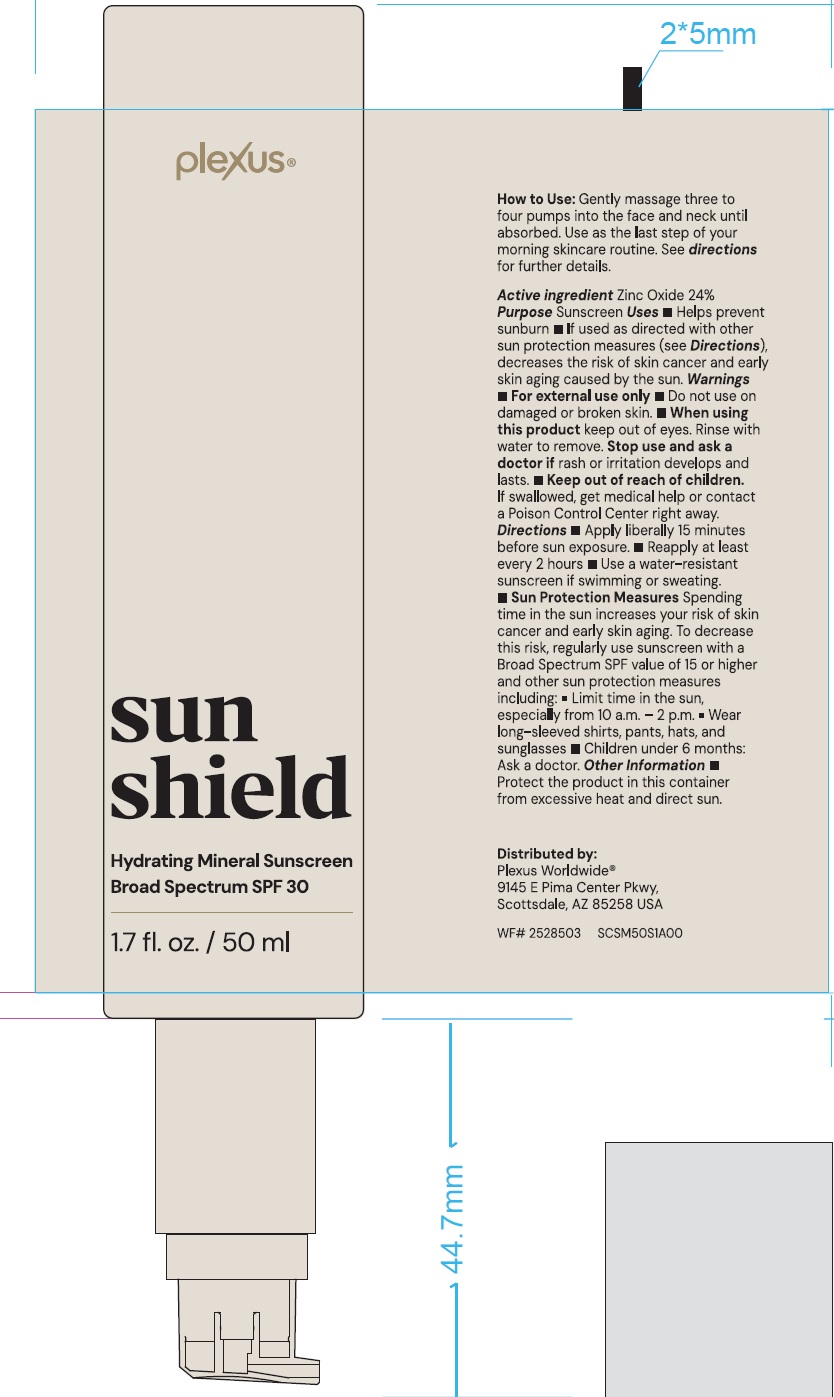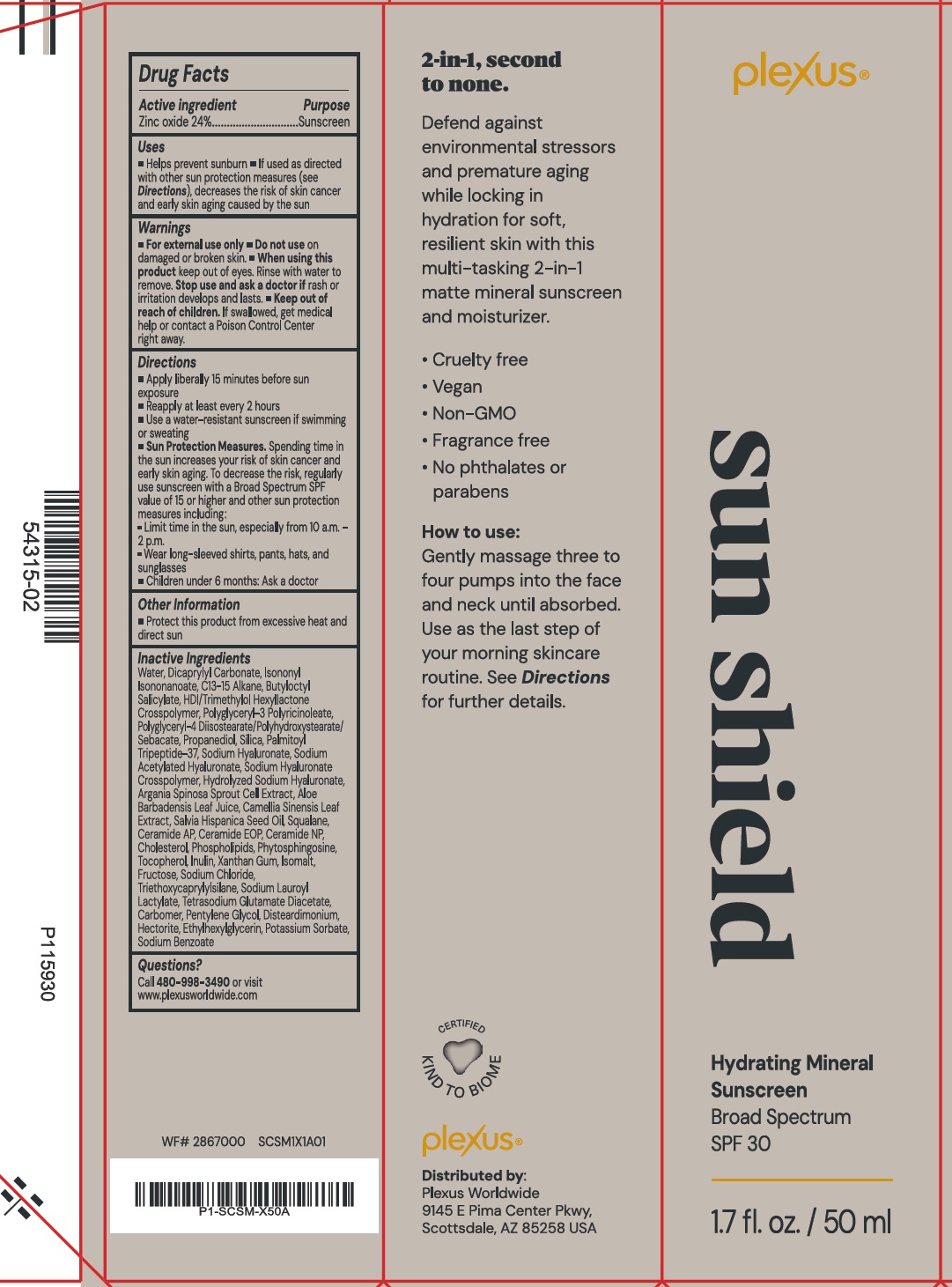 DRUG LABEL: Plexus Sun Shield Hydrating Mineral Sunscreen SPF 30
NDC: 85532-157 | Form: CREAM
Manufacturer: Plexus Worldwide, LLC
Category: otc | Type: HUMAN OTC DRUG LABEL
Date: 20250930

ACTIVE INGREDIENTS: ZINC OXIDE 240 mg/1 mL
INACTIVE INGREDIENTS: WATER; DICAPRYLYL CARBONATE; ISONONYL ISONONANOATE; C13-15 ALKANE; BUTYLOCTYL SALICYLATE; HEXAMETHYLENE DIISOCYANATE/TRIMETHYLOL HEXYLLACTONE CROSSPOLYMER; SEBACATE DIANION; PROPANEDIOL; SILICON DIOXIDE; SODIUM HYALURONATE; SODIUM ACETYLATED HYALURONATE; ALOE VERA LEAF JUICE; GREEN TEA LEAF; CHIA SEED OIL; SQUALANE; CERAMIDE AP; CERAMIDE NP; CHOLESTEROL; PHYTOSPHINGOSINE; TOCOPHEROL; INULIN; XANTHAN GUM; ISOMALT; FRUCTOSE; SODIUM CHLORIDE; TRIETHOXYCAPRYLYLSILANE; SODIUM LAUROYL LACTYLATE; TETRASODIUM GLUTAMATE DIACETATE; CARBOMER HOMOPOLYMER, UNSPECIFIED TYPE; PENTYLENE GLYCOL; HECTORITE; ETHYLHEXYLGLYCERIN; POTASSIUM SORBATE; SODIUM BENZOATE

Plexus Sun Shield Hydrating Mineral Sunscreen SPF 30

Active ingredient

Zinc Oxide 24%

Purpose

Sunscreen

Uses

- Helps prevent sunburn
- If used as directed with other sun protection measures (see Directions), decreases the risk of skin cancer and early skin aging caused by the sun

Warnings

For external use only

Do not use

- on damaged or broken skin.

When using this product

keep out of eyes. Rinse with water to remove.

Stop use and ask a doctor if

rash or irritation develops and lasts.

Keep out of reach of children.

- If swallowed, get medical help or contact a Poison Control Center right away.

Directions

- Apply liberally 15 minutes before sun exposure
- Reapply at least every 2 hours
- Use a water-resistant sunscreen if swimming or sweating
- Sun Protection Measures.Spending time in the sun increases your risk of skin cancer and early skin aging. To decrease the risk, regularly use sunscreen with a Broad Spectrum SPF value of 15 or higher and other sun protection measures including:
- Limit time in the sun, especially from 10 a.m. - 2 p.m.
- Wear long-sleeved shirts, pants, hats, and sunglasses
- Children under 6 months: Ask a doctor

Other Information

- Protect this product from excessive heat and direct sun

Inactive Ingredients

Water, Dicaprylyl Carbonate, Isononyl Isononanoate, C13-15 Alkane, Butyloctyl Salicylate, HDI/TrimethyloI Hexyllactone Crosspolymer, Polyglyceryl-3 Polyricinoleate, PolyglyceryI-4 Diisostearate/Polyhydroxystearate/ Sebacate, Propanediol, Silica, Palmitoyl Tripeptide-37, Sodium Hyaluronate, Sodium Acetylated Hyaluronate, Sodium Hyaluronate Crosspolymer, Hydrolyzed Sodium Hyaluronate, Argania Spinosa Sprout Cell Extract, Aloe Barbadensis Leaf Juice, Camellia Sinensis Leaf Extract, Salvia Hispanica Seed Oil, Squalane, Ceramide AP, Ceramide EOP, Ceramide NP, Cholesterol, Phospholipids, Phytosphingosine, Tocopherol, Inulin, Xanthan Gum, Isomalt, Fructose, Sodium Chloride, Triethoxycaprylylsilane, Sodium Lauroyl Lactylate, Tetrasodium Glutamate Diacetate, Carbomer, Pentylene Glycol, Disteardimonium, Hectorite, Ethylhexylglycerin, Potassium Sorbate, Sodium Benzoate

Questions?

Call 480-998-3490or visit
www.plexusworldwide.com